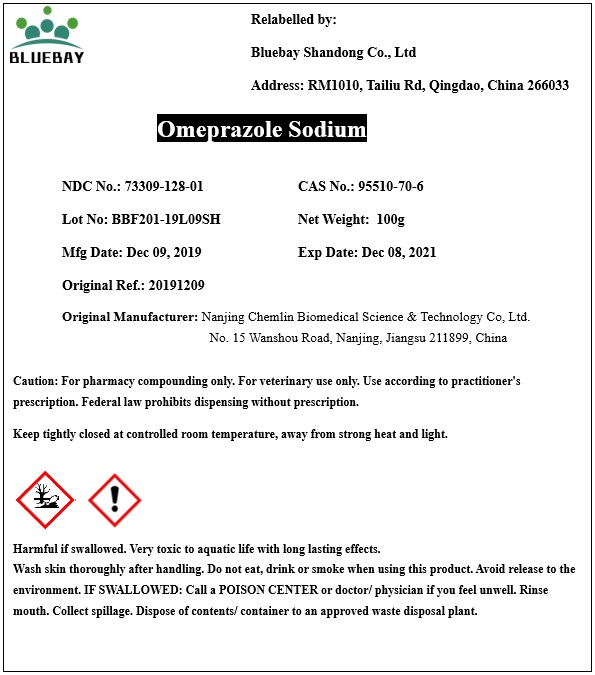 DRUG LABEL: Omeprazole Sodium
NDC: 73309-128 | Form: POWDER
Manufacturer: BLUEBAY SHANDONG CO.,LTD
Category: other | Type: BULK INGREDIENT
Date: 20200424

ACTIVE INGREDIENTS: OMEPRAZOLE SODIUM 1 g/1 g

Omeprazole Sodium